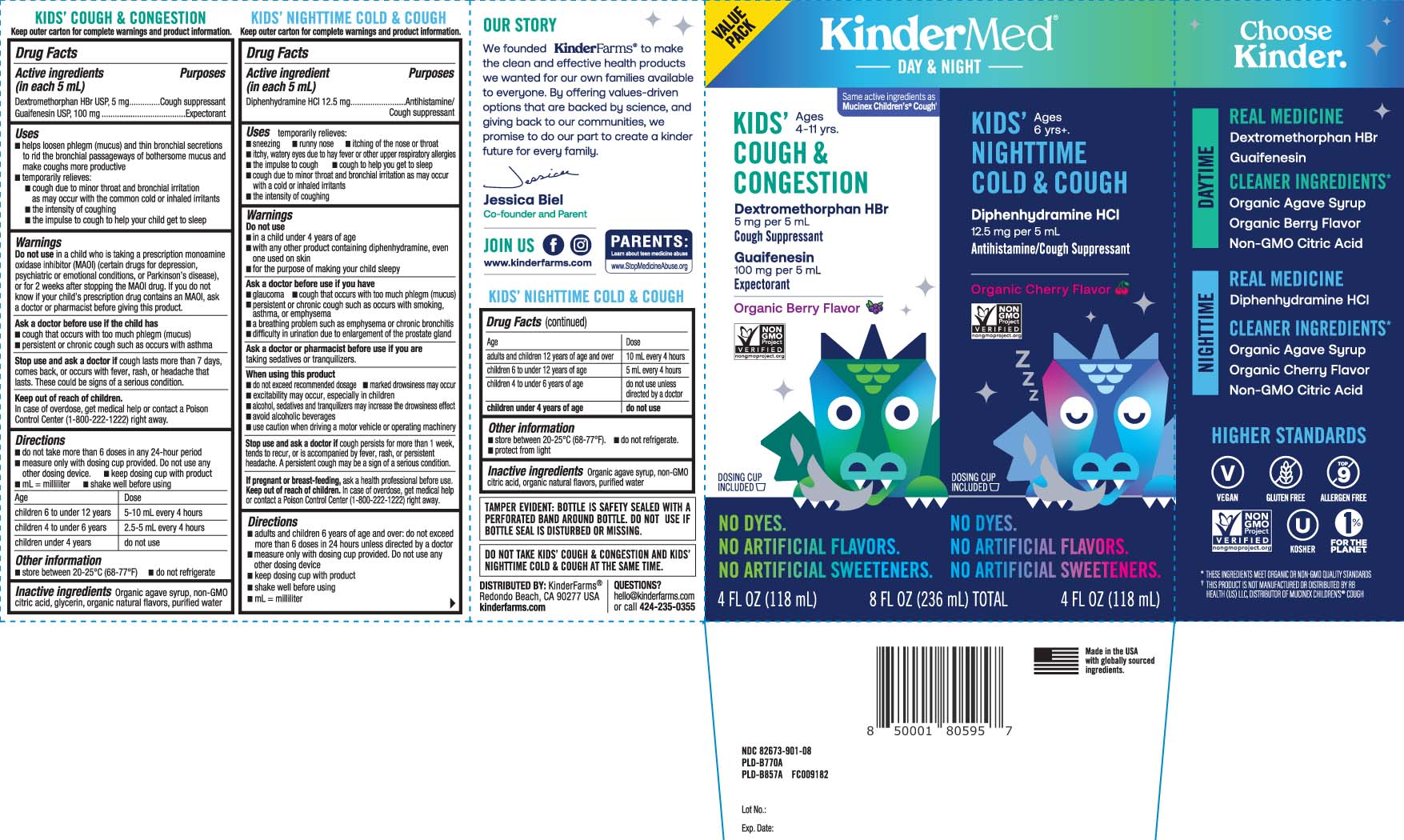 DRUG LABEL: Daytime Cough Congestion Nighttime Cold Cough
NDC: 82673-901 | Form: KIT | Route: ORAL
Manufacturer: KinderFarms, LLC
Category: otc | Type: HUMAN OTC DRUG LABEL
Date: 20240912

ACTIVE INGREDIENTS: DEXTROMETHORPHAN HYDROBROMIDE 5 mg/5 mL; GUAIFENESIN 100 mg/5 mL; DIPHENHYDRAMINE HYDROCHLORIDE 12.5 mg/5 mL
INACTIVE INGREDIENTS: AGAVE TEQUILANA JUICE; CITRIC ACID MONOHYDRATE; GLYCERIN; WATER; AGAVE TEQUILANA JUICE; CITRIC ACID MONOHYDRATE; WATER

Drug Facts

Active ingredient Daytime (in each 5 mL)

Dextromethorphan HBr USP, 5 mg

Guaifenesin USP, 100 mg

Active ingredient Nighttime (in each 5 mL)

Diphenhydramine HCl 12.5 mg

Purposes for Day Time

Cough suppressant

Expectorant

Purposes for Night Time

Antihistamine/Cough suppressant

Uses

Daytime

- helps loosen phlegm (mucus) and thin bronchial secretions to rid the bronchial passageways of bothersome mucus and make coughs more productive
- temporarily relieves
  - cough due to minor throat and bronchial irritation as may occur with the common cold or inhaled irritants
  - the intensity of coughing
  - the impulse to cough to help your child get to sleep

Nighttime

- temporarily relieves:
  - sneezing
  - runny nose
  - itching of the nose or throat
  - itchy, watery eyes due to hay fever or other upper respiratory allergies
  - the impulse to cough
  - cough to help you get to sleep
  - cough due to minor throat and bronchial irritation as may occur with cold or inhaled irritants
  - the intensity of coughing

Warnings

Do not use

DAYTIME

in a child who is taking a prescription monoamine oxidase inhibitor (MAOI) (certan drugs for depression, psychiatric or emotional conditions, or Parkinson's disease), or for 2 weeks after stopping the MAOI drug. If you do not know if your childs prescription drug contains an MAOI, ask a doctor or pharmacist before giving this product.

NIGHTTIME

- in a child under 4 years of age
- with any other product containing diphenhydramine even one used on the skin
- for the purpose of making your child sleepy

Ask a doctor before use your child has

DAYTIME

- cough that occurs with too much phlegm (mucus)
- persistent or chronic cough such occurs with asthma

NIGHTTIME

- glaucoma
- cough that occurs with too much phlegm (mucus)
- persistent or chronic cough such as occur with smoking, asthma, or emphysema
- a breathing problem such as emphysema or chronic bronchitis
- difficulty in urination due to enlargement of the prostate gland

Ask a doctor or pharmacist before use if the child is

NIGHTTIME

taking sedatives or tranquilizers.

When using this product

Nighttime

- do not exceed recommended dosage
- marked drowsiness may occur
- excitability may occur, especially in children
- alcohol, sedatives and tranquilizers may increase the drowsiness effect
- avoid alcoholic beverages
- use caution when driving a motor vehicle or operating machinery

Stop use and ask a doctor if

DAYTIME

cough lasts more than 7 days, comes back, or occurs with a fever, rash, or headache that lasts.These could be signs of a serious condition.

NIGHTTIME

cough persists for more than 1 weeks, tend to recur, or is accompanied by fever, rash or persistent headache. A persistent cough may be a sign of a serious condition

If pregnant or breast-feeding,

ask a health professional before use.

Keep out of reach of children.

Daytime

In case of overdose, get medical help or contact a Poison Control Center (1-800-222-1222) right away.

Nighttime

In case of overdose, get medical help or contact a Poison Control Center (1-800-222-1222) right away.

Directions

Daytime

- do not take more than 6 doses in any 24-hour period
- measure only with dosing cup provided. Do not use any other dosing device.
- keep dosing cup with product
- mL = milliliter
- shake well before using

age | dose
children 6 to under 12 years | 5-10 mL every 4 hours
children 4 to under 6 years | 2.5-5 mL every 4 hours
children under 4 years | do not use

Nighttime

- adults and children 6 years and over: do not exceed more than 6 doses in 24 hour unless directed by a doctor
- measure only with dosing cup provided. Do not use any other dosing device
- keep dosing cup with product
- shake well before using
- mL = milliliter

Age | Dose
adults and children 12 years of age and over | 10 mL every 4 hours
children 6 to under 12 years of age | 5 mL every 4 hours
children 4 to under 6 years of age | do not use unless directed by a doctor
children under 4 years of age | do not use

Other information

Daytime

- store between 20-25ºC (68º-77ºF).
- Do not refrigerate.

Nighttime

- store between 20-25ºC (68-77ºF).
- Do not refrigerate
- protect from light

Inactive ingredients

Day Time

Organic agave syrup, non-GMO citric acid, glycerin, organic natural flavors, purified water

Night Time

Organic agave syrup, non-GMO citric acid, organic natural flavors, purified water

Questions or comments?

Call 424-235-0355

Principal Display Panel

Same active ingredients as Mucinex Children's® Cough†

KIDS' COUGH & CONGESTION Ages 4-11 yrs

Dextromethorphan HBr 5 mg per 5 mL

Cough Suppressant

Guaifenesin 100 mg per 5 mL

Expectorant

Organic Berry Flavor

DOSING CUP INCLUDED

FL OZ (mL)

keep outer carton for complete warnings and product information

KIDS' Ages 6+

NIGHTTIME

COLD & COUGH

Diphenhydramine HCl 12.5 mg per 5 mL

Antihistamine/Cough Suppressant

Organic Cherry Flavor

DOSING CUP INCLUDED

fl oz (mL)

DO NOT TAKE KIDS' COUGH & CONGESTION AND KIDS' NIGHTTIME COLD & COUGH AT THE SAME TIME.

TAMPER EVIDENT: BOTTLE IS SAFETY SEALED WITH A PERFORATED BAND AROUND BOTTLE. DO NOT USE IF BOTTLE SEAL IS DISTURBED OR MISSING.

.†THIS PRODUCT IS NOT MANUFACTURED OR DISTRIBUTED BY RB HEALTH (US) LLC, DISTRIBUTOR OF MUCINEX CHILDREN'S® COUGH

DISTRIBUTED BY: KinderFarm®

Redondo Beach, CA 90277

Product Label

KINDERMED Kids Cough & Congestion Kids Nighttime Cold & Cough